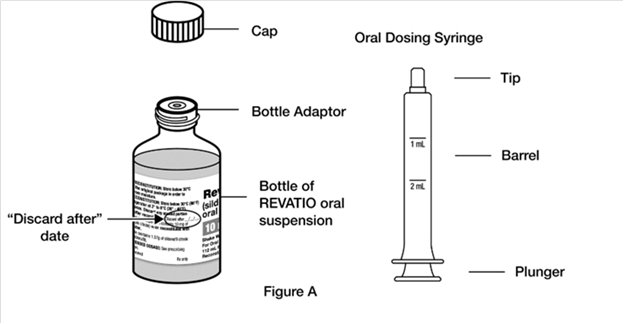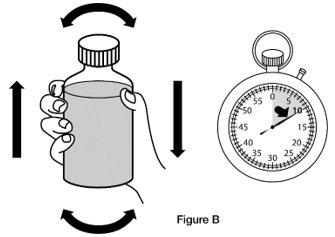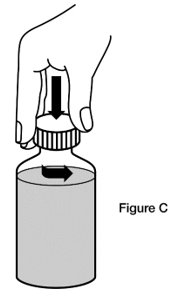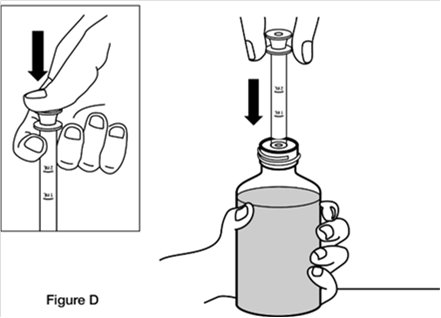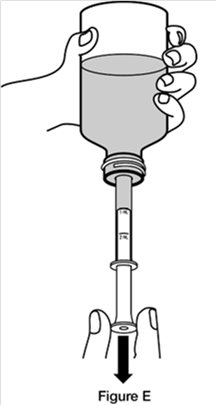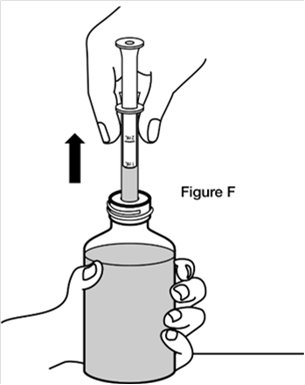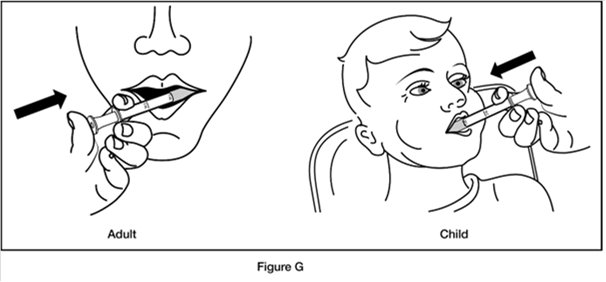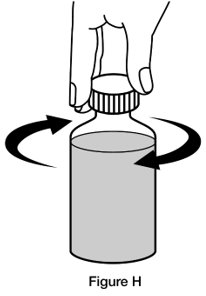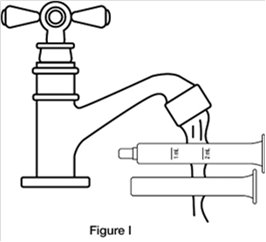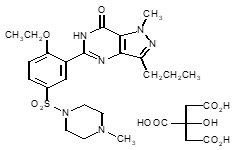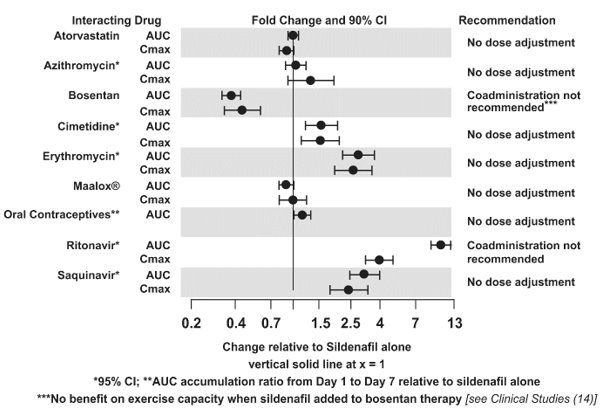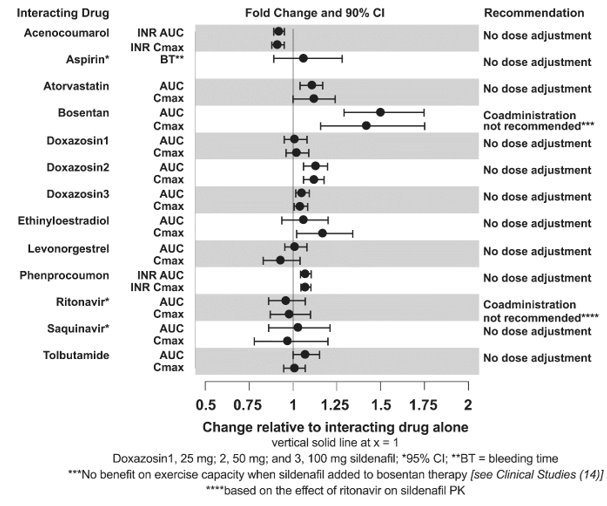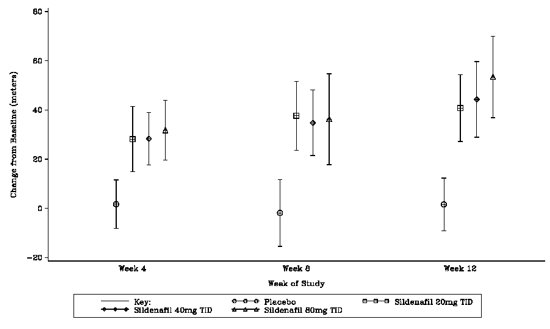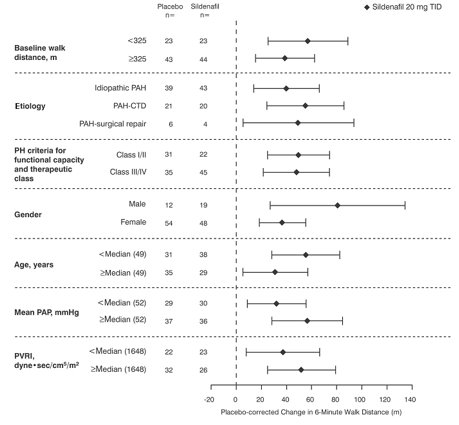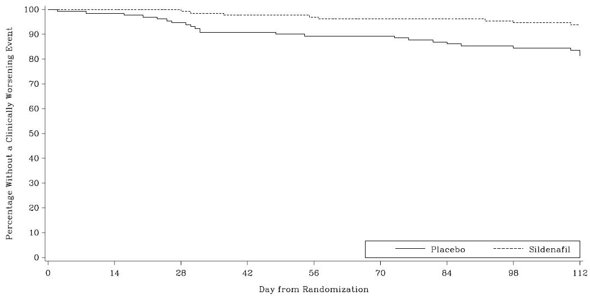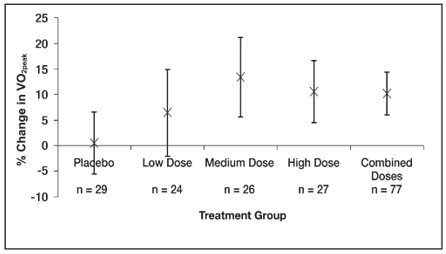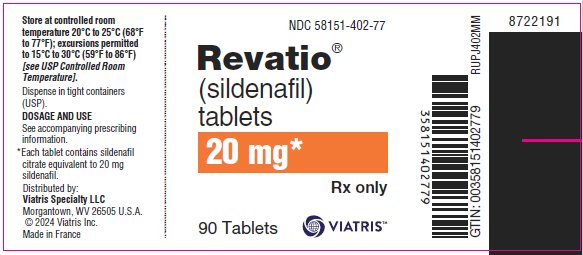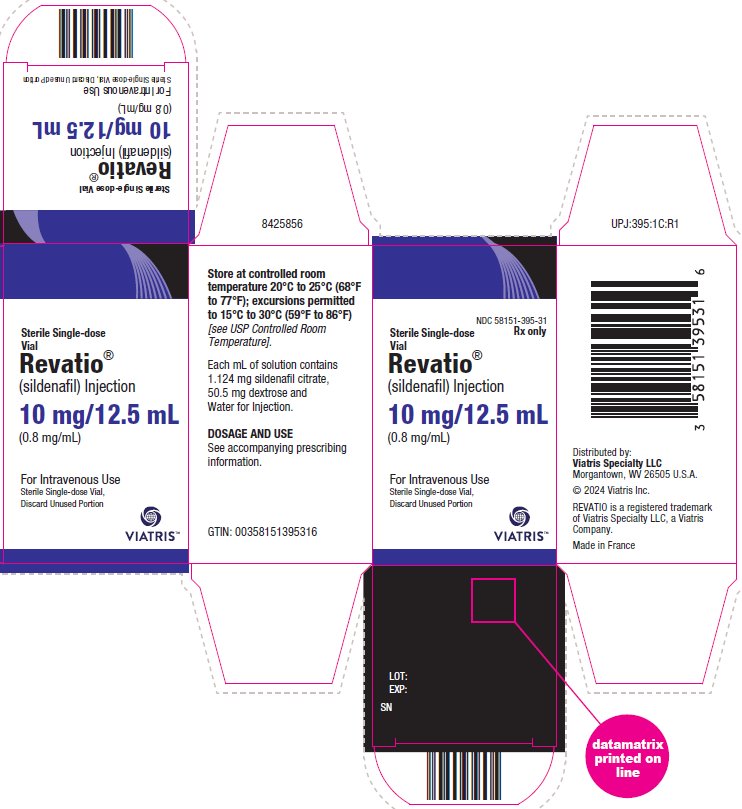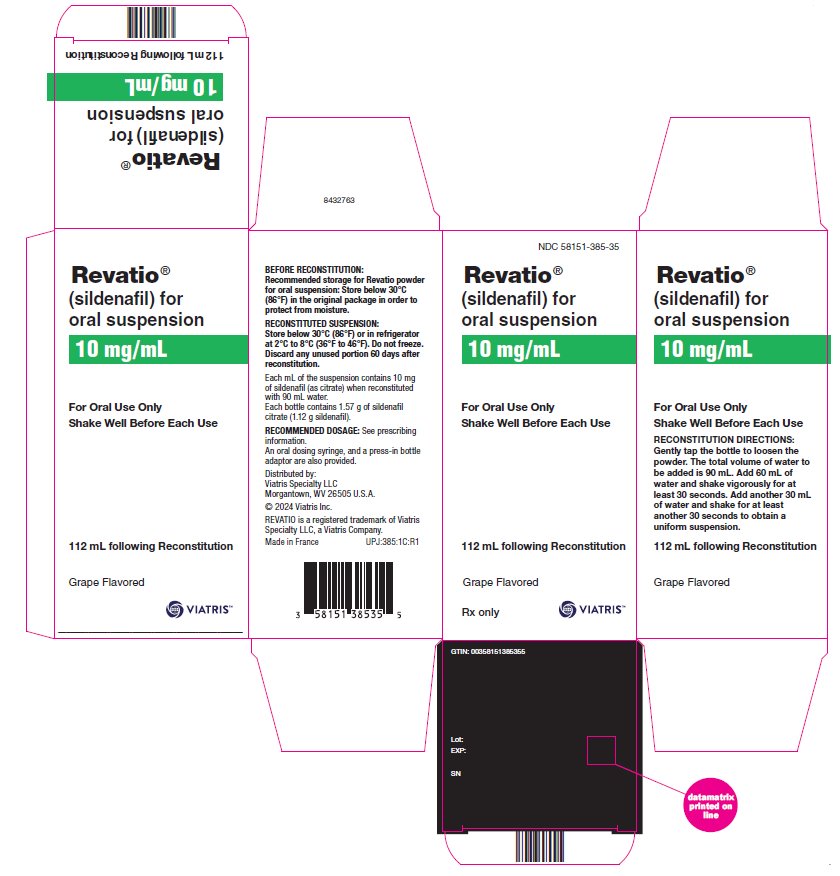 DRUG LABEL: Revatio
NDC: 58151-402 | Form: TABLET, FILM COATED
Manufacturer: Viatris Specialty LLC
Category: prescription | Type: HUMAN PRESCRIPTION DRUG LABEL
Date: 20241218

ACTIVE INGREDIENTS: SILDENAFIL CITRATE 20 mg/1 1
INACTIVE INGREDIENTS: ANHYDROUS DIBASIC CALCIUM PHOSPHATE; CROSCARMELLOSE SODIUM; HYPROMELLOSE, UNSPECIFIED; LACTOSE MONOHYDRATE; MAGNESIUM STEARATE; MICROCRYSTALLINE CELLULOSE; TITANIUM DIOXIDE; TRIACETIN

HIGHLIGHTS OF PRESCRIBING INFORMATION

These highlights do not include all the information needed to use REVATIO safely and effectively. See full prescribing information for REVATIO.
REVATIO (sildenafil) tablets, for oral use
REVATIO (sildenafil) for oral suspension
REVATIO (sildenafil) injection, for intravenous use
Initial U.S. Approval: 1998

1 INDICATIONS AND USAGE

Adults
REVATIO is a phosphodiesterase-5 (PDE-5) inhibitor indicated for the treatment of pulmonary arterial hypertension (PAH) (World Health Organization [WHO] Group I) in adults to improve exercise ability and delay clinical worsening. (1)

Pediatric Patients (1 to 17 years old)
REVATIO is indicated in pediatric patients 1 to 17 years old for the treatment of pulmonary arterial hypertension (PAH) (WHO Group I) to improve exercise ability and, in pediatric patients too young to perform standard exercise testing, pulmonary hemodynamics thought to underlie improvements in exercise (1, 14)

2 DOSAGE AND ADMINISTRATION

- Adults: 20 mg orally three times a day. Dose may be increased based on symptoms and tolerability. (2.1)
- Pediatric patients (2.2)
  - ≤ 20 kg: 10 mg three times a day
  - 20 kg to 45 kg: 20 mg three times a day
  - > 45 kg: 20 mg three times a day. Dose may be increased based on symptoms and tolerability.
- Injection (Adults): 10 mg three times a day administered as an intravenous bolus injection. (2.1)

3 DOSAGE FORMS AND STRENGTHS

- Tablets: 20 mg (3)
- For oral suspension: 10 mg/mL (when reconstituted) (3)
- Injection: 10 mg/12.5 mL (0.8 mg/mL) in a single-dose vial (3)

4 CONTRAINDICATIONS

- Use with organic nitrates or riociguat. (4)
- History of hypersensitivity reaction to sildenafil or any component of the tablet, injection, or oral suspension. (4)

5 WARNINGS AND PRECAUTIONS

- Vasodilation effects may be more common in patients with hypotension or on antihypertensive therapy. (5.1)
- Use in pulmonary veno-occlusive disease (PVOD) may cause pulmonary edema and is not recommended. (5.2)
- Hearing or visual impairment: Seek medical attention if sudden decrease or loss of vision or hearing occurs. (5.4, 5.5)
- Pulmonary hypertension (PH) secondary to sickle cell disease: REVATIO may cause serious vaso-occlusive crises. (5.8)

6 ADVERSE REACTIONS

Adults: Headache, dyspepsia, flushing, pain in limb, myalgia, back pain and diarrhea. (6.1, 6.2)

Children: Priapism. (6.1)

To report SUSPECTED ADVERSE REACTIONS, contact Viatris at 1-877-446-3679 (1-877-4-INFO-RX) or FDA at 1-800-FDA-1088 or www.fda.gov/medwatch.

7 DRUG INTERACTIONS

- Use with strong CYP3A inhibitors: Not recommended. (7, 12.3)
- Concomitant PDE-5 inhibitors: Avoid use with Viagra® or other PDE-5 inhibitors. (5.6)

FULL PRESCRIBING INFORMATION

1 INDICATIONS AND USAGE

Adults

REVATIO is indicated for the treatment of pulmonary arterial hypertension (PAH) (World Health Organization [WHO] Group I) in adults to improve exercise ability and delay clinical worsening [see Clinical Studies (14)].

Pediatric Patients (1 to 17 Years Old)

REVATIO is indicated in pediatric patients 1 to 17 years old for the treatment of pulmonary arterial hypertension (PAH) (WHO Group I) to improve exercise ability and, in pediatric patients too young to perform standardized exercise testing, pulmonary hemodynamics thought to underlie improvements in exercise [see Clinical Studies (14)].

2 DOSAGE AND ADMINISTRATION

2.1 Recommended Dosage in Adults

Oral Dosage

The recommended dosage of REVATIO is 20 mg three times a day. Dose may be titrated to a maximum of 80 mg three times a day, if required, based on symptoms and tolerability [see Clinical Studies (14)].

Although dose-response improvement in exercise ability was not observed in short-term studies in adults with PAH, the delay in clinical worsening with long-term use of sildenafil in Study A1481324 supports dosing up to a maximum of 80 mg three times a day [see Clinical Studies (14)].

Intravenous Dosage

The recommended dose is 10 mg administered as an intravenous bolus injection three times a day. The dose of REVATIO injection does not need to be adjusted for body weight.

A 10-mg dose of REVATIO injection is predicted to provide pharmacological effect of sildenafil and its N-desmethyl metabolite equivalent to that of a 20-mg oral dose.

2.2 Recommended Dosage in Pediatric Patients

Oral Dosage

The recommended dosage in patients ≤ 20 kg is 10 mg three times a day.

For pediatric patients 20 kg to 45 kg, the recommended dosage is 20 mg three times a day.

For pediatric patients 45 kg and greater, the recommended dosage is 20 mg three times a day. A maximum dose in pediatric patients has not been identified. Based on the experience in adults, dose may be titrated to a maximum of 40 mg three times a day for pediatric patients > 45 kg, if required, based on symptoms and tolerability [see Clinical Studies (14)].

2.3 Reconstitution of the Powder for Oral Suspension

Note: Reconstitute the contents of the bottle with a total volume of 90 mL (60 mL followed by 30 mL). Refer to the detailed instructions below.

1. Tap the bottle to loosen the powder.
2. Add 60 mL of water to the bottle.
3. Replace the cap and shake the bottle vigorously for a minimum of 30 seconds.
4. Add another 30 mL of water to the bottle.
5. Replace the cap and shake the bottle vigorously for a minimum of 30 seconds.
6. Remove cap and press the bottle adaptor into the neck of the bottle. Replace the cap on the bottle.
7. Write the expiration date of the reconstituted oral suspension on the bottle label (the expiration date of the reconstituted oral suspension is 60 days from the date of reconstitution).

Incompatibilities

Do not mix with any other medication or additional flavoring agent.

3 DOSAGE FORMS AND STRENGTHS

REVATIO Tablets

White to off-white, film-coated, round tablets engraved with “RVT 20” on one side and “VLE” on the other side. Each tablet contains sildenafil citrate equivalent to 20 mg of sildenafil.

REVATIO for Oral Suspension

White to slight pink powder containing 1.57 g of sildenafil citrate (equivalent to 1.12 g sildenafil) in a bottle for reconstitution to 10 mg/mL. Following reconstitution with 90 mL of water, the total volume of the oral suspension is 112 mL. A 2 mL oral dosing syringe (with 1 mL and 2 mL dose markings) and a press-in bottle adaptor are also provided.

REVATIO Injection

Single-dose vial containing 10 mg/12.5 mL (0.8 mg/mL) of sildenafil.

4 CONTRAINDICATIONS

REVATIO is contraindicated in patients with:

- Concomitant use of organic nitrates in any form, either regularly or intermittently, because of the greater risk of hypotension [see Warnings and Precautions (5.1)].
- Concomitant use of riociguat, a guanylate cyclase stimulator. Phosphodiesterase-5 (PDE-5) inhibitors, including sildenafil, may potentiate the hypotensive effects of riociguat.
- Known hypersensitivity to sildenafil or any component of the tablet, injection, or oral suspension. Hypersensitivity, including anaphylactic reaction, anaphylactic shock and anaphylactoid reaction, has been reported in association with the use of sildenafil.

5 WARNINGS AND PRECAUTIONS

5.1 Hypotension

REVATIO has vasodilatory properties, resulting in mild and transient decreases in blood pressure. Before prescribing REVATIO, carefully consider whether patients with certain underlying conditions could be adversely affected by such vasodilatory effects (e.g., patients on antihypertensive therapy or with resting hypotension [blood pressure less than 90/50], fluid depletion, severe left ventricular outflow obstruction, or autonomic dysfunction). Monitor blood pressure when co‑administering blood pressure lowering drugs with REVATIO.

5.2 Worsening Pulmonary Vascular Occlusive Disease

Pulmonary vasodilators may significantly worsen the cardiovascular status of patients with pulmonary veno-occlusive disease (PVOD). Since there are no clinical data on administration of REVATIO to patients with veno-occlusive disease, administration of REVATIO to such patients is not recommended. Should signs of pulmonary edema occur when REVATIO is administered, consider the possibility of associated PVOD.

5.3 Epistaxis

The incidence of epistaxis was 13% in patients taking REVATIO with PAH secondary to CTD. This effect was not seen in idiopathic PAH (REVATIO 3%, placebo 2%) patients. The incidence of epistaxis was also higher in REVATIO-treated patients with a concomitant oral vitamin K antagonist (9% versus 2% in those not treated with concomitant vitamin K antagonist).

The safety of REVATIO is unknown in patients with bleeding disorders or active peptic ulceration.

5.4 Visual Loss

When used to treat erectile dysfunction, non-arteritic anterior ischemic optic neuropathy (NAION), a cause of decreased vision including permanent loss of vision, has been reported post marketing in temporal association with the use of PDE-5 inhibitors, including sildenafil. Most patients had underlying anatomic or vascular risk factors for developing NAION, including low cup to disc ratio (“crowded disc”).

Advise patients to seek immediate medical attention in the event of a sudden loss of vision in one or both eyes while taking REVATIO.

There are no controlled clinical data on the safety or efficacy of REVATIO in patients with retinitis pigmentosa, a minority of whom have genetic disorders of retinal phosphodiesterases. Therefore, use of REVATIO in patients with retinitis pigmentosa is not recommended.

5.5 Hearing Loss

Cases of sudden decrease or loss of hearing, which may be accompanied by tinnitus and dizziness, have been reported in temporal association with the use of PDE-5 inhibitors, including REVATIO. In some of the cases, medical conditions and other factors were reported that may have played a role. In many cases, medical follow-up information was limited. It is not possible to determine whether these reported events are related directly to the use of REVATIO, to the patient’s underlying risk factors for hearing loss, a combination of these factors, or to other factors.

Advise patients to seek prompt medical attention in the event of sudden decrease or loss of hearing while taking PDE-5 inhibitors, including REVATIO.

5.6 Combination with Other PDE-5 Inhibitors

Sildenafil is also marketed as VIAGRA®. The safety and efficacy of combinations of REVATIO with VIAGRA or other PDE‑5 inhibitors have not been studied. Inform patients taking REVATIO not to take VIAGRA or other PDE‑5 inhibitors.

5.7 Priapism

Use REVATIO with caution in patients with anatomical deformation of the penis (e.g., angulation, cavernosal fibrosis, or Peyronie’s disease) or in patients who have conditions, which may predispose them to priapism (e.g., sickle cell anemia, multiple myeloma, or leukemia). In the event of an erection that persists longer than 4 hours, the patient should seek immediate medical assistance. If priapism (painful erection greater than 6 hours in duration) is not treated immediately, penile tissue damage and permanent loss of potency could result.

5.8 Vaso-occlusive Crisis in Patients with Pulmonary Hypertension Secondary to Sickle Cell Disease

In a small, prematurely terminated study of patients with pulmonary hypertension (PH) secondary to sickle cell disease, vaso-occlusive crises requiring hospitalization were more commonly reported by patients who received REVATIO than by those randomized to placebo. The effectiveness and safety of REVATIO in the treatment of PH secondary to sickle cell disease has not been established.

6 ADVERSE REACTIONS

The following serious adverse events are discussed elsewhere in the labeling:

- Hypotension [see Warnings and Precautions (5.1)]
- Vision Loss [see Warnings and Precautions (5.4)]
- Hearing Loss [see Warnings and Precautions (5.5)]
- Priapism [see Warnings and Precautions (5.7)]
- Vaso-occlusive Crisis in Patients with Pulmonary Hypertension Secondary to Sickle Cell Disease [see Warnings and Precautions (5.8)]

6.1 Clinical Trials Experience

Because clinical trials are conducted under widely varying conditions, adverse reaction rates observed in the clinical trials of a drug cannot be directly compared to rates in the clinical trials of another drug and may not reflect the rates observed in practice.

In a 12-week, placebo-controlled clinical study and an open-label extension study (SUPER-1) in 277 REVATIO-treated adults with PAH (WHO Group I) [see Clinical Studies (14)] the adverse reactions that were reported by at least 10% of REVATIO-treated patients in any dosing group, and were more frequent in REVATIO-treated patients than in placebo-treated patients are shown in Table 1. Adverse reactions were generally transient and mild to moderate in nature. The overall frequency of discontinuation in REVATIO-treated patients was 3% (20 mg and 40 mg three times a day) and 8% (80 mg three times a day). The overall frequency of discontinuation for placebo was 3%.

Table 1. Most Common Adverse Reactions in Patients Treated with REVATIO 20 mg, 40 mg, 80 mg and Placebo Three Times Per Day in SUPER-1 (More Frequent in REVATIO-Treated Patients than Placebo-Treated Patients)
 | REVATIO; 20 mg; (n = 69) | REVATIO; 40 mg; (n = 67) | REVATIO; 80 mg; (n = 71) | Placebo; (n = 70)
Headache | 46% | 42% | 49% | 39%
Flushing | 10% | 9% | 16% | 4%
Pain in Limb | 7% | 15% | 9% | 6%
Myalgia | 7% | 6% | 14% | 4%
Back Pain | 13% | 13% | 9% | 11%
Dyspepsia | 13% | 8% | 13% | 7%
Diarrhea | 9% | 12% | 10% | 6%

In a placebo-controlled fixed dose titration study (PACES-1) of REVATIO (starting with recommended dose of 20 mg and increased to 40 mg and then 80 mg all three times a day) as an adjunct to intravenous epoprostenol in patients with PAH, no new safety issues were identified except for edema, which occurred in 25% of subjects in the combined REVATIO + epoprostenol group compared with 13% of subjects in the epoprostenol group [see Clinical Studies (14)].

In a study to assess the effects of multiple doses of REVATIO on mortality in adults with PAH (StudyA1481324), the lower dose 5 mg TID group showed a higher observed number of deaths (all related to underlying disease/disease under study), serious adverse events, and severe adverse events than the 20 mg and 80 mg TID groups [see Clinical Studies (14)]. Overall, the safety data for sildenafil 80 mg TID dose in Study A1481324 was consistent with the established safety profile of sildenafil in previous adult PAH studies.

Pediatric Patients

REVATIO was studied in a total of 234 PAH pediatric patients 1 to 17 years of age in a 16‑week, double-blind placebo‑controlled study (STARTS-1); 220 patients continued in a long-term extension study (STARTS-2). Erection increased was observed in 9% of patients treated with sildenafil in STARTS-1. No other new adverse reactions were identified in pediatric patients [see Use in Specific Populations (8.4)].

REVATIO Injection

Adverse events with REVATIO injection were similar to those seen with oral tablets.

6.2 Postmarketing Experience

The following adverse reactions have been identified during post approval use of sildenafil (marketed for both PAH and erectile dysfunction). Because these reactions are reported voluntarily from a population of uncertain size, it is not always possible to reliably estimate their frequency or establish a causal relationship to drug exposure.

Cardiovascular Events

In postmarketing experience with sildenafil at doses indicated for erectile dysfunction, serious cardiovascular, cerebrovascular, and vascular events, including myocardial infarction, sudden cardiac death, ventricular arrhythmia, cerebrovascular hemorrhage, transient ischemic attack, hypertension, pulmonary hemorrhage, and subarachnoid and intracerebral hemorrhages have been reported in temporal association with the use of the drug. Most, but not all, of these patients had preexisting cardiovascular risk factors. Many of these events were reported to occur during or shortly after sexual activity, and a few were reported to occur shortly after the use of sildenafil without sexual activity. Others were reported to have occurred hours to days after use concurrent with sexual activity. It is not possible to determine whether these events are related directly to sildenafil, to sexual activity, to the patient’s underlying cardiovascular disease, or to a combination of these or other factors.

Nervous System

Seizure, seizure recurrence

Ophthalmologic

NAION [see Warnings and Precautions (5.4), Patient Counseling Information (17)].

7 DRUG INTERACTIONS

Nitrates

Concomitant use of REVATIO with nitrates in any form is contraindicated [see Contraindications (4)].

Strong CYP3A Inhibitors

Concomitant use of REVATIO with strong CYP3A inhibitors is not recommended [see Clinical Pharmacology (12.3)].

Moderate-to-Strong CYP3A Inducers

Concomitant use of REVATIO with moderate-to-strong CYP3A inducers (such as bosentan) decreases the sildenafil exposure. Dose up-titration of REVATIO may be needed when initiating treatment with moderate-to-strong CYP3A inducers. Reduce the dose of REVATIO to 20 mg three times a day when discontinuing treatment with moderate-to-strong CYP3A inducers [see Clinical Pharmacology (12.3) and Clinical Studies (14)].

8 USE IN SPECIFIC POPULATIONS

8.1 Pregnancy

Risk Summary

Limited published data from randomized controlled trials, case-controlled trials, and case series do not report a clear association with sildenafil and major birth defects, miscarriage, or adverse maternal or fetal outcomes when sildenafil is used during pregnancy. There are risks to the mother and fetus from untreated pulmonary arterial hypertension (see Clinical Considerations). Animal reproduction studies conducted with sildenafil showed no evidence of embryo-fetal toxicity or teratogenicity at doses up to 32- and 65-times the recommended human dose (RHD) of 20 mg three times a day in rats and rabbits, respectively (see Data).

The estimated background risk of major birth defects and miscarriage for the indicated population is unknown. All pregnancies have a background risk of birth defect, loss, or other adverse outcomes. In the U.S. general population, the estimated background risk of major birth defects and miscarriage in clinically recognized pregnancies is 2-4% and 15-20%, respectively.

Clinical Considerations

Disease-Associated Maternal and/or Embryo/Fetal Risk

Pregnant women with untreated pulmonary arterial hypertension are at risk for heart failure, stroke, preterm delivery, and maternal and fetal death.

Data

Animal Data

No evidence of teratogenicity, embryotoxicity, or fetotoxicity was observed in pregnant rats or rabbits dosed with sildenafil 200 mg/kg/day during organogenesis, a level that is, on a mg/m^2 basis, 32- and 65-times, respectively, the recommended human dose (RHD) of 20 mg three times a day. In a rat pre- and postnatal development study, the no‑observed-adverse-effect dose was 30 mg/kg/day (equivalent to 5-times the RHD on a mg/m^2 basis).

8.2 Lactation

Risk Summary

Limited published data from a case report describe the presence of sildenafil and its active metabolite in human milk. There is insufficient information about the effects of sildenafil on the breastfed infant and no information on the effects of sildenafil on milk production. Limited clinical data during lactation preclude a clear determination of the risk of REVATIO to an infant during lactation.

8.4 Pediatric Use

The safety and efficacy of REVATIO have been established in pediatric patients 1 to 17 years old, for the treatment of PAH (WHO Group I) to improve exercise ability and, in patients too young to perform standard exercising testing, pulmonary hemodynamics thought to underlie improvements in exercise. Use of REVATIO for this indication is supported by evidence from adequate and well-controlled studies in adults with additional PK and safety data in pediatric patients aged 1 year and older [see Adverse Reactions (6.1), Clinical Studies (14)]. The safety and effectiveness of REVATIO have not been established in pediatric patients younger than 1 year of age.

During the conduct of the pediatric studies (STARTS-1 and STARTS-2) [see Clinical Studies (14)], an imbalance in the number of deaths was noted: 5/55 (9.1%), 10/74 (13.5%), and 22/100 (22%) in the sildenafil low, medium, and high dose groups, respectively. The causes of death were related to the progression of PAH. This safety observation in pediatrics was not confirmed in a study conducted in adults designed to evaluate this risk (Study A1481324). Given the beneficial effects on clinical worsening and death observed in adults with increasing doses (Study A1481324) and the expected similarity of disease in pediatrics and adults, a causal association for the observed dose-related effect on mortality in pediatric patients is unlikely, and therefore, the available data support dosing in pediatric patients > 45 kg up to a maximum of 40 mg three times a day.

8.5 Geriatric Use

Clinical studies of REVATIO did not include sufficient numbers of patients aged 65 and over to determine whether they respond differently from younger patients. Other reported clinical experience has not identified differences in responses between the elderly and younger patients. In general, dose selection for an elderly patient should be cautious, reflecting the greater frequency of decreased hepatic, renal, or cardiac function, and of concomitant disease or other drug therapy [see Clinical Pharmacology (12.3)].

8.6 Patients with Hepatic Impairment

No dose adjustment for mild to moderate impairment is required. Severe impairment has not been studied [see Clinical Pharmacology (12.3)].

8.7 Patients with Renal Impairment

No dose adjustment is required (including severe impairment CLcr < 30 mL/min) [see Clinical Pharmacology (12.3)].

10 OVERDOSAGE

In studies with healthy volunteers of single doses up to 800 mg, adverse events were similar to those seen at lower doses but rates and severities were increased.

In cases of overdose, standard supportive measures should be adopted as required. Renal dialysis is not expected to accelerate clearance as sildenafil is highly bound to plasma proteins and it is not eliminated in the urine.

11 DESCRIPTION

REVATIO, phosphodiesterase-5 (PDE-5) inhibitor, is the citrate salt of sildenafil, a selective inhibitor of cyclic guanosine monophosphate (cGMP)-specific phosphodiesterase type-5 (PDE-5). Sildenafil is also marketed as VIAGRA® for erectile dysfunction.

Sildenafil citrate is designated chemically as 1-[[3-(6,7-dihydro-1-methyl-7-oxo-3-propyl-1H-pyrazolo [4,3-d] pyrimidin-5-yl)-4-ethoxyphenyl] sulfonyl]-4-methylpiperazine citrate and has the following structural formula:

Sildenafil citrate is a white to off-white crystalline powder with a solubility of 3.5 mg/mL in water and a molecular weight of 666.7.

REVATIO (sildenafil) Tablets: REVATIO is formulated as white to off-white, film-coated, round tablets for oral administration. Each tablet contains sildenafil citrate equivalent to 20 mg of sildenafil. In addition to the active ingredient, sildenafil citrate, each tablet contains the following inactive ingredients: anhydrous dibasic calcium phosphate, croscarmellose sodium, hypromellose, lactose monohydrate, magnesium stearate, microcrystalline cellulose, titanium dioxide, and triacetin.

REVATIO (sildenafil) Injection: REVATIO is supplied as a clear, colorless, sterile, ready to use solution in a single-dose vial containing 10 mg/12.5 mL of sildenafil. Each mL of solution contains 1.124 mg sildenafil citrate (equivalent to 0.8 mg sildenafil), 50.5 mg dextrose, and water for injection.

REVATIO (sildenafil) for Oral Suspension: REVATIO is supplied as white to slight pink powder containing 1.57 g of sildenafil citrate (equivalent to 1.12 g sildenafil) in an amber glass bottle intended for reconstitution. Following reconstitution with 90 mL water, the total volume of the oral suspension is 112 mL and the oral suspension contains 10 mg/mL sildenafil. The inactive ingredients include citric acid anhydrous, colloidal silicon dioxide anhydrous, grape flavor, sodium benzoate, sodium citrate dihydrate, sorbitol, sucralose, titanium dioxide, and xanthan gum. In addition to the bottle, a press-in bottle adapter and an oral dosing syringe (with 1 mL and 2 mL dose markings) are provided.

12 CLINICAL PHARMACOLOGY

12.1 Mechanism of Action

Sildenafil is an inhibitor of cGMP specific PDE-5 in the smooth muscle of the pulmonary vasculature, where PDE-5 is responsible for degradation of cGMP. Sildenafil, therefore, increases cGMP within pulmonary vascular smooth muscle cells resulting in relaxation. In patients with PAH, this can lead to vasodilation of the pulmonary vascular bed and, to a lesser degree, vasodilatation in the systemic circulation.

Studies in vitro have shown that sildenafil is selective for PDE5. Its effect is more potent on PDE5 than on other known phosphodiesterases (10-fold for PDE6, greater than 80-fold for PDE1, greater than 700-fold for PDE2, PDE3, PDE4, PDE7, PDE8, PDE9, PDE10, and PDE11). The approximately 4,000-fold selectivity for PDE-5 versus PDE3 is important because PDE3 is involved in control of cardiac contractility. Sildenafil is only about 10 times as potent for PDE5 compared to PDE6, an enzyme found in the retina and involved in the phototransduction pathway of the retina. This lower selectivity is thought to be the basis for abnormalities related to color vision observed with higher doses or plasma levels [see Clinical Pharmacology (12.2)].

In addition to pulmonary vascular smooth muscle and the corpus cavernosum, PDE5 is also found in other tissues including vascular and visceral smooth muscle and in platelets. The inhibition of PDE5 in these tissues by sildenafil may be the basis for the enhanced platelet anti-aggregatory activity of nitric oxide observed in vitro, and the mild peripheral arterial-venous dilatation in vivo.

12.2 Pharmacodynamics

Effects of REVATIO on Hemodynamic Measures

Adults

Patients on all REVATIO doses achieved a statistically significant reduction in mean pulmonary arterial pressure (mPAP) compared to those on placebo in a study with no background vasodilators [see SUPER-1 in Clinical Studies (14)]. Data on other hemodynamic measures for the REVATIO 20 mg three times a day and placebo dosing regimens is displayed in Table 2. The relationship between these effects and improvements in 6-minute walk distance is unknown.

Table 2. Changes from Baseline in Hemodynamic Parameters at Week 12 [mean (95% CI)] for the REVATIO 20 mg Three Times a Day and Placebo Group
 | Placebo; (n = 65) [The number of patients per treatment group varied slightly for each parameter due to missing assessments.] | REVATIO 20 mg; (n = 65)
mPAP (mmHg) | 0.6 (-0.8, 2.0) | -2.1 (-4.3, 0.0)
PVR (dyn•s/cm^5) | 49 (-54, 153) | -122 (-217, -27)
SVR (dyn•s/cm^5) | -78 (-197, 41) | -167 (-307, -26)
RAP (mmHg) | 0.3 (-0.9, 1.5) | -0.8 (-1.9, 0.3)
CO (L/min) | -0.1 (-0.4, 0.2) | 0.4 (0.1, 0.7)
HR (beats/min) | -1.3 (-4.1, 1.4) | -3.7 (-5.9, -1.4)
mPAP = mean pulmonary arterial pressure; PVR = pulmonary vascular resistance; SVR = systemic vascular resistance; RAP = right atrial pressure; CO = cardiac output; HR = heart rate.

Pediatric Patients

Patients on REVATIO medium and high dose groups achieved dose related improvements in pulmonary vascular resistance index (PVRI) and mean pulmonary arterial pressure (mPAP) compared to those on placebo [see STARTS-1 in Clinical Studies (14)]. Improvements were observed with cardiac index in all three REVATIO dose groups over placebo. Data on other hemodynamic measures for the REVATIO low, medium and high dose groups compared to placebo is displayed in Table 3.

Table 3. Placebo Corrected Changes in Hemodynamic Parameters by Dose Group
Parameter; [Estimate (95% CI)] | Low Dose | Medium Dose | High Dose
PVRI (%) | -2% (-20%, 20%); n = 37 | -18% (-32%, -2%); n = 51 | -27% (-39%, -14%); n = 68
mPAP (mmHg) | 1.6 (-4.5, 7.6); n = 39 | -3.5 (-8.9, 1.9); n = 55 | -7.3 (-12.4, -2.1); n = 71
CI (%) | 10% (-4%, 26%); n = 37 | 4% (-7%, 18%); n = 51 | 15% (3%, 29%); n = 69
SVRI (%) | -9% (-22%, 7%); n = 37 | -5% (-17%, 10%); n = 50 | -16% (-26%, -4%); n = 68
RAP (mmHg) | -0.17 (-1.91, 1.57); n = 39 | -0.19 (-1.73, 1.36); n = 55 | -1.14 (-2.61, 0.33); n = 71
HR (%) | 3% (-5%, 12%); n = 39 | 2% (-5%, 9%); n = 55 | -2% (-9%, 5%); n = 71
Abbreviations: CI = cardiac index; HR = heart rate; mPAP = mean pulmonary arterial pressure; PVRI = pulmonary vascular resistance index; RAP = right atrial pressure; SVRI = systemic vascular resistance index.
Note: n = 52, 56, 55, 54, 56, and 56 placebo patients for PVRI, mPAP, CI, SVRI, RAP and HR, respectively.

Effects of REVATIO on Blood Pressure

Single oral doses of sildenafil 100 mg administered to healthy volunteers produced decreases in supine blood pressure (mean maximum decrease in systolic/diastolic blood pressure of 8/5 mmHg). The decrease in blood pressure was most notable approximately 1-2 hours after dosing and was not different from placebo at 8 hours. Similar effects on blood pressure were noted with 25 mg, 50 mg, and 100 mg doses of sildenafil, therefore the effects are not related to dose or plasma levels within this dosage range. Larger effects were recorded among patients receiving concomitant nitrates [see Contraindications (4)].

Single oral doses of sildenafil up to 100 mg in healthy volunteers produced no clinically relevant effects on electrocardiogram (ECG). After chronic dosing of 80 mg three times a day to patients with PAH, no clinically relevant effects on ECG were reported.

After chronic dosing of 80 mg three times a day sildenafil to healthy volunteers, the largest mean change from baseline in supine systolic and supine diastolic blood pressures was a decrease of 9.0 mmHg and 8.4 mmHg, respectively.

After chronic dosing of 80 mg three times a day sildenafil to patients with systemic hypertension, the mean change from baseline in systolic and diastolic blood pressures was a decrease of 9.4 and 9.1 mmHg, respectively.

After chronic dosing of 80 mg three times a day sildenafil to patients with PAH, lesser reductions than above in systolic and diastolic blood pressures were observed (a decrease in both of 2 mmHg).

Effects of REVATIO on Vision

At single oral doses of 100 mg and 200 mg, transient dose-related impairment of color discrimination (blue/green) was detected using the Farnsworth-Munsell 100-hue test, with peak effects near the time of peak plasma levels. This finding is consistent with the inhibition of PDE6, which is involved in phototransduction in the retina. An evaluation of visual function at doses up to 200 mg revealed no effects of REVATIO on visual acuity, intraocular pressure, or pupillometry.

12.3 Pharmacokinetics

Absorption and Distribution

REVATIO is rapidly absorbed after oral administration, with a mean absolute bioavailability of 41% (25 to 63%). Maximum observed plasma concentrations are reached within 30 to 120 minutes (median 60 minutes) of oral dosing in the fasted state. When REVATIO is taken with a high-fat meal, the rate of absorption is reduced, with a mean delay in Tmax of 60 minutes and a mean reduction in Cmax of 29%. The mean steady state volume of distribution (Vss) for sildenafil is 105 L, indicating distribution into the tissues. Sildenafil and its major circulating N-desmethyl metabolite are both approximately 96% bound to plasma proteins. Protein binding is independent of total drug concentrations.

Bioequivalence was established between the 20 mg tablet and the 10 mg/mL oral suspension when administered as a 20 mg single oral dose of sildenafil (as citrate).

Metabolism and Excretion

Sildenafil is cleared predominantly by the CYP3A (major route) and cytochrome P450 2C9 (CYP2C9, minor route) hepatic microsomal isoenzymes. The major circulating metabolite results from N-desmethylation of sildenafil, and is, itself, further metabolized. This metabolite has a phosphodiesterase selectivity profile similar to sildenafil and an in vitro potency for PDE-5 approximately 50% of the parent drug. In healthy volunteers, plasma concentrations of this metabolite are approximately 40% of those seen for sildenafil, so that the metabolite accounts for about 20% of sildenafil’s pharmacologic effects. In patients with PAH, however, the ratio of the metabolite to sildenafil is higher. Both sildenafil and the active metabolite have terminal half-lives of about 4 hours.

After either oral or intravenous administration, sildenafil is excreted as metabolites predominantly in the feces (approximately 80% of the administered oral dose) and to a lesser extent in the urine (approximately 13% of the administered oral dose).

REVATIO Injection: The pharmacokinetic profile of REVATIO has been characterized following intravenous administration. A 10 mg dose of REVATIO Injection is predicted to provide a pharmacological effect of sildenafil and its N-desmethyl metabolite equivalent to that of a 20 mg oral dose.

Population Pharmacokinetics

Age, gender, race, and renal and hepatic function were included as factors assessed in the population pharmacokinetic model to evaluate sildenafil pharmacokinetics in patients with PAH. The dataset available for the population pharmacokinetic evaluation contained a wide range of demographic data and laboratory parameters associated with hepatic and renal function. None of these factors had a significant impact on sildenafil pharmacokinetics in patients with PAH.

In patients with PAH, the average steady-state concentrations were 20 to 50% higher when compared to those of healthy volunteers. There was also a doubling of Cmin levels compared to healthy volunteers. Both findings suggest a lower clearance and/or a higher oral bioavailability of sildenafil in patients with PAH compared to healthy volunteers.

Pediatric Patients

Body weight was shown to be a good predictor of drug exposure in children. Sildenafil plasma concentration half-life values were estimated to range from 2.9 to 4.4 hours for a range of 10 to 70 kg of body weight. Tmax was estimated at approximately 1 hour.

Geriatric Patients

Healthy elderly volunteers (65 years or over) had a reduced clearance of sildenafil, resulting in approximately 84% and 107% higher plasma concentrations of sildenafil and its active N-desmethyl metabolite, respectively, compared to those seen in healthy younger volunteers (18 to 45 years). Due to age-differences in plasma protein binding, the corresponding increase in the AUC of free (unbound) sildenafil and its active N-desmethyl metabolite were 45% and 57%, respectively.

Renal Impairment

In volunteers with mild (CLcr = 50-80 mL/min) and moderate (CLcr = 30-49 mL/min) renal impairment, the pharmacokinetics of a single oral dose of sildenafil (50 mg) was not altered. In volunteers with severe (CLcr less than 30 mL/min) renal impairment, sildenafil clearance was reduced, resulting in approximately doubling of AUC and Cmax compared to age-matched volunteers with no renal impairment. In addition, N-desmethyl metabolite AUC and Cmax values were significantly increased 200% and 79%, respectively, in patients with severe renal impairment compared to patients with normal renal function.

Hepatic Impairment

In volunteers with mild to moderate hepatic cirrhosis (Child-Pugh class A and B), sildenafil clearance was reduced, resulting in increases in AUC (84%) and Cmax (47%) compared to age-matched volunteers with no hepatic impairment. Patients with severe hepatic impairment (Child-Pugh class C) have not been studied.

Drug Interaction Studies

In vitro Studies

Sildenafil metabolism is principally mediated by the CYP3A (major route) and CYP2C9 (minor route) cytochrome P450 isoforms. Therefore, inhibitors of these isoenzymes may reduce sildenafil clearance and inducers of these isoenzymes may increase sildenafil clearance.

Sildenafil is a weak inhibitor of the cytochrome P450 isoforms 1A2, 2C9, 2C19, 2D6, 2E1 and 3A (IC50 greater than150 µM).

Sildenafil is not expected to affect the pharmacokinetics of compounds which are substrates of these CYP enzymes at clinically relevant concentrations.

In vivo Studies

The effects of other drugs on sildenafil pharmacokinetics and the effects of sildenafil on the exposure to other drugs are shown in Figure 1 and Figure 2, respectively.

Figure 1. Effects of Other Drugs on Sildenafil Pharmacokinetics

Figure 2. Effects of Sildenafil on Other Drugs

CYP3A Inhibitors and Beta Blockers

Population pharmacokinetic analysis of data from patients in clinical trials indicated an approximately 30% reduction in sildenafil clearance when it was co-administered with mild/moderate CYP3A inhibitors and an approximately 34% reduction in sildenafil clearance when co-administered with beta-blockers. Sildenafil exposure at a dose of 80 mg three times a day without concomitant medication is shown to be 5-fold the exposure at a dose of 20 mg three times a day. This concentration range covers the same increased sildenafil exposure observed in specifically‑designed drug interaction studies with CYP3A inhibitors (except for potent inhibitors such as ketoconazole, itraconazole, and ritonavir).

REVATIO Injection: Predictions based on a pharmacokinetic model suggest that drug-drug interactions with CYP3A inhibitors will be less than those observed after oral sildenafil administration.

CYP3A4 Inducers Including Bosentan

Concomitant administration of strong CYP3A inducers is expected to cause substantial decreases in plasma levels of sildenafil.

Population pharmacokinetic analysis of data from patients in clinical trials indicated approximately 3-fold the sildenafil clearance when it was co-administered with mild CYP3A inducers.

Epoprostenol

The mean reduction of sildenafil (80 mg three times a day) bioavailability when co-administered with epoprostenol was 28%, resulting in about 22% lower mean average steady state concentrations. Therefore, the slight decrease of sildenafil exposure in the presence of epoprostenol is not considered clinically relevant. The effect of sildenafil on epoprostenol pharmacokinetics is not known.

No significant interactions were shown with tolbutamide (250 mg) or warfarin (40 mg), both of which are metabolized by CYP2C9.

Alcohol

Sildenafil (50 mg) did not potentiate the hypotensive effect of alcohol in healthy volunteers with mean maximum blood alcohol levels of 0.08%.

13 NONCLINICAL TOXICOLOGY

13.1 Carcinogenesis, Mutagenesis, Impairment of Fertility

Sildenafil was not carcinogenic when administered to rats for up to 24 months at 60 mg/kg/day, a dose resulting in total systemic exposure (AUC) to unbound sildenafil and its major metabolite 33- and 37-times, for male and female rats, respectively, the human exposure at the RHD of 20 mg three times a day. Sildenafil was not carcinogenic when administered to male and female mice for up to 21 and 18 months, respectively, at doses up to a maximally tolerated level of 10 mg/kg/day, a dose equivalent to the RHD on a mg/m^2 basis.

Sildenafil was negative in in vitro bacterial and Chinese hamster ovary cell assays to detect mutagenicity, and in vitro human lymphocytes and in vivo mouse micronucleus assays to detect clastogenicity.

There was no impairment of fertility in male or female rats given up to 60 mg sildenafil/kg/day, a dose producing a total systemic exposure (AUC) to unbound sildenafil and its major metabolite of 19- and 38-times for males and females, respectively, the human exposure at the RHD of 20 mg three times a day.

14 CLINICAL STUDIES

SUPER-1 (NCT00644605) - REVATIO Monotherapy [20 mg, 40 mg, and 80 mg Three Times a Day]

A randomized, double-blind, placebo-controlled study of REVATIO (SUPER-1) was conducted in 277 patients with PAH (defined as a mean pulmonary artery pressure ≥ 25 mmHg at rest with a pulmonary capillary wedge pressure < 15 mmHg). Patients were predominantly WHO Functional Classes II-III. Allowed background therapy included a combination of anticoagulants, digoxin, calcium channel blockers, diuretics, and oxygen. The use of prostacyclin analogues, endothelin receptor antagonists, and arginine supplementation were not permitted. Patients who had failed to respond to bosentan were also excluded. Patients with left ventricular ejection fraction less than 45% or left ventricular shortening fraction less than 0.2 also were not studied.

Patients were randomized to receive placebo (n = 70) or REVATIO 20 mg (n = 69), 40 mg (n = 67) or 80 mg (n = 71) three times a day for a period of 12 weeks. They had either primary pulmonary hypertension (PPH) (63%), PAH associated with CTD (30%), or PAH following surgical repair of left-to-right congenital heart lesions (7%). The study population consisted of 25% men and 75% women with a mean age of 49 years (range: 18 to 81 years) and baseline 6-minute walk distance between 100 and 450 meters (mean 343).

The primary efficacy endpoint was the change from baseline at Week 12 (at least 4 hours after the last dose) in the 6-minute walk distance. Placebo-corrected mean increases in walk distance of 45-50 meters were observed with all doses of REVATIO. These increases were significantly different from placebo, but the REVATIO dose groups were not different from each other (see Figure 3), indicating no additional clinical benefit from doses higher than 20 mg three times a day. The improvement in walk distance was apparent after 4 weeks of treatment and was maintained at Week 8 and Week 12.

Figure 3. Change from Baseline in 6-Minute Walk Distance (meters) at Weeks 4, 8, and 12 in SUPER-1: Mean (95% Confidence Interval)

Figure 4 displays subgroup efficacy analyses in SUPER-1 for the change from baseline in 6-Minute Walk Distance at Week 12 including baseline walk distance, disease etiology, functional class, gender, age, and hemodynamic parameters.

Figure 4. Placebo-Corrected Change from Baseline in 6-Minute Walk Distance (meters) at Week 12 by Study Subpopulation in SUPER-1: Mean (95% Confidence Interval)

Key: PAH = pulmonary arterial hypertension; CTD = connective tissue disease; PH = pulmonary hypertension; PAP = pulmonary arterial pressure; PVRI = pulmonary vascular resistance index; TID = three times daily.

SUPER-2 (NCT00159887) Long-Term Treatment of PAH

In a long-term follow-up of patients who were treated with sildenafil (n = 277), K-M estimates of survival at 1, 2, and 3 years were 94%, 88% , and 79%, respectively. These uncontrolled observations do not allow comparison with a group not given sildenafil and cannot be used to determine the long term-effect of sildenafil on mortality.

PACES-1 (NCT00159861) - REVATIO Co-Administered with Epoprostenol

A randomized, double-blind, placebo‑controlled study (PACES-1) was conducted in 267 patients with PAH who were taking stable doses of intravenous epoprostenol. Patients had to have a mean pulmonary artery pressure (mPAP) greater than or equal to 25 mmHg and a pulmonary capillary wedge pressure (PCWP) less than or equal to 15 mmHg at rest via right heart catheterization within 21 days before randomization, and a baseline 6-minute walk test distance greater than or equal to 100 meters and less than or equal to 450 meters (mean 349 meters). Patients were randomized to placebo or REVATIO (in a fixed titration starting from 20 mg to 40 mg and then 80 mg, three times a day) and all patients continued intravenous epoprostenol therapy.

At baseline patients had PPH (80%) or PAH secondary to CTD (20%); WHO Functional Class I (1%), II (26%), III (67%), or IV (6%); and the mean age was 48 years, 80% were female, and 79% were Caucasian.

There was a statistically significant greater increase from baseline in 6-minute walk distance at Week 16 (primary endpoint) for the REVATIO group compared with the placebo group. The mean change from baseline at Week 16 (last observation carried forward) was 30 meters for the REVATIO group compared with 4 meters for the placebo group giving an adjusted treatment difference of 26 meters (95% CI: 10.8, 41.2) (p = 0.0009).

Patients on REVATIO achieved a statistically significant reduction in mPAP compared to those on placebo. A mean placebo-corrected treatment effect of -3.9 mmHg was observed in favor of REVATIO (95% CI: -5.7, -2.1) (p = 0.00003).

Time to clinical worsening of PAH was defined as the time from randomization to the first occurrence of a clinical worsening event (death, lung transplantation, initiation of bosentan therapy, or clinical deterioration requiring a change in epoprostenol therapy). Table 4 displays the number of patients with clinical worsening events in PACES-1. Kaplan-Meier estimates and a stratified log-rank test demonstrated that placebo-treated patients were 3 times more likely to experience a clinical worsening event than REVATIO-treated patients and that REVATIO-treated patients experienced a significant delay in time to clinical worsening versus placebo-treated patients (p = 0.0074). Kaplan‑Meier plot of time to clinical worsening is presented in Figure 5.

Table 4. Clinical Worsening Events in PACES-1
 | Placebo; (N = 131) |  | REVATIO; (N = 134)
Number of patients with clinical worsening first event | 23 |  | 8
 | First Event | All Events | First Event | All Events
Death, n | 3 | 4 | 0 | 0
Lung transplantation, n | 1 | 1 | 0 | 0
Hospitalization due to PAH, n | 9 | 11 | 8 | 8
Clinical deterioration resulting in: Change of Epoprostenol Dose, n; Initiation of Bosentan, n | 9; 1 | 16; 1 | 0; 0 | 2; 0
Proportion worsened; 95% Confidence Interval | 0.187; (0.12-0.26) |  | 0.062; (0.02-0.10)

Figure 5. Kaplan-Meier Plot of Time (in Days) to Clinical Worsening of PAH in PACES-1

Improvements in WHO Functional Class for PAH were also demonstrated in patients on REVATIO compared to placebo. More than twice as many REVATIO-treated patients (36%) as placebo-treated patients (14%) showed an improvement in at least one functional New York Heart Association (NYHA) class for PAH.

Study A1481243 (NCT00323297) - REVATIO Added to Bosentan Therapy – Lack of Effect on Exercise Capacity

A randomized, double-blind, placebo‑controlled study was conducted in 103 patients with PAH who were on bosentan therapy for a minimum of 3 months. The PAH patients included those with primary PAH and PAH associated with CTD. Patients were randomized to placebo or sildenafil (20 mg three times a day) in combination with bosentan (62.5 to 125 mg twice a day). The primary efficacy endpoint was the change from baseline at Week 12 in 6-minute walk distance (6MWD). The results indicate that there is no significant difference in mean change from baseline on 6MWD observed between sildenafil 20 mg plus bosentan and bosentan alone.

STARTS-1 (NCT00159913) - Sildenafil in Treatment-Naive Children, Aged 1 to 17 Years, with Pulmonary Arterial Hypertension

A total of 234 patients with PAH aged 1 to 17 years were treated in a randomized, double-blind, multi-center, placebo-controlled parallel group, dose-ranging study. Patients (38% male and 62% female) had body weight ≥ 8 kg and had idiopathic pulmonary arterial hypertension (33%), or PAH associated with congenital heart disease (systemic-to-pulmonary shunt 37%, surgical repair 30%). In this trial, 27% of patients were < 7 years old. Patients were WHO Functional Class I (32%), II (51%), III (15%), or IV (0.4%).

Patients were naïve for specific PAH therapy and the use of prostacyclin, prostacyclin analogues and endothelin receptor antagonists were not permitted in the study, and neither were arginine supplementation, nitrates, alpha-blockers and potent CYP450 3A4 inhibitors.

The primary objective of the study was to assess the effect of REVATIO on percent change from baseline in PVO2, normalized to body weight, from baseline to week 16 as measured by the Cardiopulmonary Exercise Test (CPET) (patients who were developmentally able to perform the test, n = 115). Secondary endpoints included hemodynamic monitoring, symptom assessment, WHO Functional Class, change in background treatment, and quality of life measurements (n = 234).

Patients were allocated to one of three sildenafil treatment groups (low, medium, or high) or placebo. Actual doses administered were dependent on body weight (see Table 5).

Table 5. Treatment Allocation by Dose and Body Weight in Pediatric Study
 | Placebo | Low Dose |  | Medium Dose |  | High Dose
Body Weight (kg) | N | Dose | N | Dose | N | Dose | N
≥ 8-20 | 18 |  | na | 10 mg | 15 | 20 mg | 35
> 20-45 | 32 | 10 mg | 31 | 20 mg | 30 | 40 mg | 31
> 45 | 10 | 10 mg | 11 | 40 mg | 10 | 80 mg | 11

The proportion of patients receiving supportive medicinal products at baseline (anticoagulants, digoxin, calcium channel blockers, diuretics and/or oxygen) was similar in the combined sildenafil treatment group (48%) and the placebo treatment group (42%).

The primary endpoint was a percentage change in VO2peak from baseline to week 16 assessed by CPET. Mean baseline peak volume of oxygen consumed (VO2) values were similar across the sildenafil treatment groups (17 to 18 mL/kg/min), and slightly higher for the placebo treatment group (20 mL/kg/min). See Figure 6.

A total of 45% of patients were evaluable for CPET, which comprised those children ≥ 7 years old and developmentally able to perform the test. Children < 7 years were evaluable only for the secondary endpoints.

Mean increases in VO2peak percentage change from baseline at Week 16, were observed with all 3 sildenafil doses (range of 6% to 13%, Figure 6), with little change with placebo (0.5%).

Figure 6. Percentage Change from Baseline in VO2Peak: Mean (95% Confidence Intervals)

The estimated difference between the combined sildenafil doses and placebo was 8% (95% CI: -0.2 to 16). The results of the main analysis (combined dose groups versus placebo) were not statistically significant (p = 0.056).

The estimated difference between the sildenafil medium dose group and placebo was 11 ± 5% (95% CI: 2 to 21).

Impact on Hemodynamic Parameters

Dose related improvements were observed with PVRI and mPAP. Statistically significant PVRI reductions compared to placebo were seen with the sildenafil medium and high dose groups (18% [95% CI: -32% to -2%] and 27% [95% CI: -39% to -14%], respectively) but not the low dose group (2% (95% CI: -20%, 20%). The sildenafil medium and high dose groups displayed mPAP changes from baseline compared to placebo, of ‑3.5 mmHg (95% CI: ‑8.9, 1.9) and ‑7.3 mmHg (95% CI: ‑12.4, ‑2.1), respectively; while the low dose group showed little difference from placebo (difference of 1.6 mmHg [95% CI: -4.5, 7.6]). Improvements were observed with cardiac index with all three sildenafil groups over placebo, 10%, 4%, and 15% for the low, medium, and high dose groups, respectively [see Clinical Pharmacology (12.2)].

STARTS-2 (NCT00159874) - Long-Term Survival with Oral Sildenafil Monotherapy in Treatment-Naïve Pediatric Pulmonary Arterial Hypertension

Of the 234 pediatric patients treated in the short-term, placebo-controlled study, 220 patients entered the long-term extension study. Patients who had been in the placebo group in the short-term study were randomly reassigned to sildenafil treatment; patients weighing ≤ 20 kg entered the medium or high dose groups (1:2), while patients weighing > 20 kg entered the low, medium, or high dose groups (1:1:1). Of the total 229 patients who received sildenafil, there were 55, 74, and 100 patients in the low, medium, and high dose groups, respectively. Across the short-term and long-term studies, the overall duration of treatment from start of double-blind for individual patients ranged from 3 to 3,129 days. By sildenafil treatment group, median duration of sildenafil treatment was 1,696 days (excluding the 5 patients who received placebo in double-blind and were not treated in the long-term extension study).

Peak VO2 was assessed 1 year after the start of the placebo-controlled study. Of sildenafil-treated patients developmentally able to perform the CPET 59/114 patients (52%) had not shown any deterioration in PVO2 from start of sildenafil. Similarly, 191 of 229 patients (83%) who had received sildenafil had either maintained or improved their WHO Functional Class at 1 year assessment.

Kaplan-Meier estimates of survival at 3 years in patients > 20 kg in weight at baseline were 94%, 93%, and 85% in the low, medium, and high dose groups, respectively; for patients ≤ 20 kg in weight at baseline, the survival estimates were 94% and 93% for patients in the medium and high dose groups, respectively [see Use in Specific Populations (8.4) and Adverse Reactions (6.1)].

Study A1481324 (NCT02060487) - Study to Assess the Effects of REVATIO on Mortality in Adults with PAH

A study to assess the effects of multiple doses of sildenafil on mortality in adults with PAH was conducted following the observation of a higher risk of mortality in pediatric patients taking a high dose of REVATIO TID, based on body weight, compared to those taking a lower dose of REVATIO in the long-term extension of the pediatric clinical trial.

The study was a randomized, double-blind, parallel-group study in 385 adults with PAH. Patients were randomly assigned 1:1:1 to one of three treatment groups (5, 20, and 80 mg TID). Most patients were PAH treatment naïve (83%). For most patients the etiology of PAH was idiopathic (72%). The most common WHO Functional Class was Class III (58% of patients). Treatment groups were well balanced with respect to baseline demographics of strata history of PAH treatment and etiology of PAH, as well as the WHO Functional Class categories.

The primary objective of the study was to compare sildenafil 80 mg TID versus 5 mg TID for mortality, with success defined by ruling out twice the mortality at 80 mg.

The key secondary efficacy endpoint was time to first event of clinical worsening, defined as a composite endpoint of all-cause mortality, hospitalization for worsening PAH or disease progression. An additional secondary endpoint was 6MWD at Months 6 and 12.

Overall Survival

At the time of a planned interim analysis (50% deaths) it was identified that the primary efficacy objective of this protocol was met and therefore the study was stopped. Based on the primary efficacy endpoint (mortality), the non-inferiority of sildenafil 80 mg TID arm versus 5 mg TID arm was met using a 2-sided significance level of 0.003 for the interim analysis. Primary comparison of the 80 mg TID group to the 5 mg TID group yielded the HR (99.7% CI) = 0.51 (0.22, 1.21); i.e., non-inferiority was established.

Table 6. Hazard Ratios for Overall Survival, Assessed in the Proportional Hazards Model – Intent To Treat Population
 | Sildenafil 5 mg N = 129 | Sildenafil 20 mg N = 128 | Sildenafil 80 mg N = 128
Patient‑years of follow‑up | 329.8 | 340.5 | 356.7
Number of deaths (%) | 34 (26) | 25 (20) | 19 (15)
On treatment deaths [On treatment deaths: Any death within 7 days of last dose was regarded as “On treatment”, thus might include deaths occurred after discontinuation from study treatment.] (%) | 22 (17) | 13 (10) | 15 (12)
Off treatment deaths (%) | 12 (9) | 12 (9) | 4 (3)
Hazard ratio relative to sildenafil 5 mg
Hazard ratio estimate [Hazard ratio estimates from the proportional Hazards model, stratified by actual previous PAH treatment and etiology of PAH.] |  | 0.68 | 0.51
99.7% CI |  | 0.31, 1.49 | 0.22, 1.21
Hazard ratio relative to sildenafil 20 mg
Hazard ratio estimate |  |  | 0.74
99.7% CI |  |  | 0.30, 1.84

Kaplan-Meier estimates of survival at 3 years were 66%, 79%, and 85% in the 5-, 20-, and 80-mg TID dose groups, respectively.

Clinical Worsening

Sildenafil 80 mg was also superior to 5 mg for time to first event of clinical worsening with HR (99.7% CI) = 0.44 (0.22, 0.89).

Table 7. Hazard Ratios for Time to First Event of Clinical Worsening – Intent To Treat Population
 | Sildenafil 5 mg N = 129 | Sildenafil 20 mg N = 128 | Sildenafil 80 mg N = 128
Patient‑years of follow‑up | 249.6 | 276.4 | 306.5
Number of patients with clinical worsening | 52 | 36 | 28
First Event of clinical worsening [Clinical worsening events were defined as reduction from baseline in the 6MWD test by at least 15% and worsening functional class from baseline, both confirmed by a second test/evaluation within 2 weeks.] n (%)
Disease progression [Count of cases of disease progression as the first event of clinical worsening.] | 8 (6) | 2 (2) | 6 (5)
Hospitalization for PAH [Count of non-elective hospital stays for worsening PAH as the first event of clinical worsening.] | 28 (22) | 23 (18) | 11 (9)
Death [Count of deaths as the first event of clinical worsening.] | 16 (12) | 11 (9) | 11 (9)
Hazard ratio relative to sildenafil 5 mg
Hazard ratio estimate |  | 0.63 | 0.44
99.7% CI |  | 0.33, 1.21 | 0.22, 0.89
p-value |  | 0.035 | < 0.001
Hazard ratio relative to sildenafil 20 mg
Hazard ratio estimate [Hazard ratio estimates from the proportional Hazards model, stratified by actual previous PAH treatment and etiology of PAH. P-value from the Wald test.] |  |  | 0.72
99.7% CI |  |  | 0.34, 1.52
p‑value |  |  | 0.195
Note: Sildenafil 5 mg is not an approved dosage.
Abbreviations: 6MWD = 6‑minute walk distance; CI = confidence interval; PAH = pulmonary arterial hypertension.

6MWD at Months 6 and 12

At baseline, the median of 6MWD for the intent‑to‑treat (ITT) population was 332 to 352 m. At Month 6, the median change from baseline was highest for sildenafil 80 mg TID with 28 m compared to 18 m and 19 m for sildenafil 5 mg TID and sildenafil 20 mg TID groups, respectively. The same was seen at Month 12, the median change from baseline for sildenafil 80 mg TID group was 33 m compared to 17 m for sildenafil 5 mg TID and 31 m in sildenafil 20 mg TID groups.

Overall, the safety data for sildenafil 20 mg TID and for the higher sildenafil 80 mg TID dose were consistent with the established safety profile of sildenafil in previous adult PAH studies [see Adverse Reactions (6.1)].

16 HOW SUPPLIED/STORAGE AND HANDLING

REVATIO tablets are supplied as white to off-white, film-coated, round tablets containing sildenafil citrate equivalent to the nominally indicated amount of sildenafil as follows:

REVATIO Tablets
Package Configuration | Strength | NDC | Engraving on Tablet
Bottle of 90 Tablets | 20 mg | 58151-402-77 | “RVT 20” on one side and “VLE” on the other side

Recommended Storage for REVATIO Tablets: Store at controlled room temperature 20°C to 25°C (68°F to 77°F); excursions permitted to 15°C to 30°C (59°F to 86°F) [see USP Controlled Room Temperature].

REVATIO injection is supplied as a clear, colorless, sterile, ready to use solution containing 10 mg sildenafil/12.5 mL (0.8 mg/mL) presented in a single-dose glass vial.

REVATIO Injection
Package Configuration | Strength | NDC
Vial individually packaged in a carton | 10 mg/12.5 mL (0.8 mg/mL) | 58151-395-31

Recommended Storage for REVATIO Injection: Store at controlled room temperature 20°C to 25°C (68°F to 77°F); excursions permitted to 15°C to 30°C (59°F to 86°F) [see USP Controlled Room Temperature]. Discard unused portion.

REVATIO powder for oral suspension is supplied in amber glass bottles. Each bottle contains white to slight pink powder containing 1.57 g of sildenafil citrate (equivalent to 1.12 g sildenafil). Following reconstitution, the total volume of the oral suspension is 112 mL (10 mg sildenafil/mL). A 2 mL oral dosing syringe (with 1 mL and 2 mL dose markings) and a press-in bottle adaptor are also provided.

REVATIO Powder for Oral Suspension
Package Configuration | Strength | NDC
Powder for oral suspension - bottle | 10 mg/mL (when reconstituted) | 58151-385-35

Recommended Storage for REVATIO for Oral Suspension: Store below 30°C (86°F) in the original package in order to protect from moisture.

Recommended Storage for Reconstituted Oral Suspension: Store below 30°C (86°F) or in refrigerator at 2°C to 8°C (36°F to 46°F). Do not freeze. The shelf-life of the reconstituted oral suspension is 60 days. Any remaining oral suspension should be discarded 60 days after reconstitution.

17 PATIENT COUNSELING INFORMATION

Advise the patient to read the FDA-approved patient labeling (Patient Information and Instructions for Use).

- Inform patients of contraindication of REVATIO with regular and/or intermittent use of organic nitrates.
- Inform patients that sildenafil is also marketed as VIAGRA for erectile dysfunction. Advise patients taking REVATIO not to take VIAGRA or other PDE-5 inhibitors.
- Advise patients to seek immediate medical attention for a sudden loss of vision in one or both eyes while taking REVATIO. Such an event may be a sign of NAION.
- Advise patients to seek prompt medical attention in the event of sudden decrease or loss of hearing while taking REVATIO. These events may be accompanied by tinnitus and dizziness.

Distributed by:
Viatris Specialty LLC
Morgantown, WV 26505 U.S.A.

© 2024 Viatris Inc.

REVATIO is a registered trademark of Viatris Specialty LLC, a Viatris Company.

UPJ:RVTTOSI:R2

PATIENT INFORMATION

REVATIO® (re-VAH-tee-oh)

(sildenafil)

tablets

REVATIO® (re-VAH-tee-oh)

(sildenafil)

oral suspension

What is the most important information I should know about REVATIO?

Never take REVATIO with any nitrate or guanylate cyclase stimulator medicines.

- Your blood pressure could drop quickly to an unsafe level.

Nitrates include:

- Medicines that treat chest pain (angina)
- Nitroglycerin in any form including tablets, patches, sprays, and ointments
- Isosorbide mononitrate or dinitrate
- Street drugs called “poppers” (amyl nitrate, butyl nitrate or nitrite)

Guanylate cyclase stimulators include:

- Riociguat, a medicine that treats pulmonary arterial hypertension and chronic thromboembolic pulmonary hypertension.

Ask your healthcare provider or pharmacist if you are not sure if you or your child are taking a nitrate or a guanylate cyclase stimulator medicine.

See “What are the possible side effects of REVATIO?” for more information about side effects.

What is REVATIO?

REVATIO is a prescription medicine used to treat pulmonary arterial hypertension (PAH). PAH is a type of high blood pressure in the arteries of your lungs. REVATIO may be used in:

- adults to improve your ability to exercise and help slow down the worsening of your physical condition.
- children 1 to 17 years old to improve their ability to exercise, and in children too young to do certain exercise and lung testing.

It is not known if REVATIO is safe and effective in children younger than 1 year of age.

Do not take REVATIO if you or your child:

- take medicines called nitrates.
- take riociguat, a guanylate cyclase stimulator medicine.
- are allergic to sildenafil or any of the ingredients in REVATIO. See the end of this leaflet for a complete list of ingredients in REVATIO.

Before taking REVATIO, tell your healthcare provider about all of your medical conditions, including if you or your child:

- have low blood pressure
- have heart problems
- have pulmonary veno-occlusive disease (PVOD)
- have bleeding problems or a stomach (peptic) ulcer. It is not known if REVATIO is safe in people with bleeding problems or who have a stomach ulcer.
- have an eye problem called retinitis pigmentosa
- have ever had sudden loss of vision in one or both eyes, including an eye problem called non-arteritic anterior ischemic optic neuropathy (NAION)
- have ever had hearing problems such as ringing in the ears, dizziness, or loss of hearing
- have a deformed penis shape or Peyronie’s disease
- have any blood cell problems such as sickle cell anemia
- are pregnant or plan to become pregnant. It is not known if REVATIO will harm your unborn baby.
- are breastfeeding or plan to breastfeed. REVATIO passes into your breast milk. It is not known if it can harm your baby. Talk with your healthcare provider about the best way to feed your baby during treatment with REVATIO.

Tell your healthcare provider about all of the medicines you or your child take, including prescription and over-the-counter medicines, vitamins, and herbal supplements. REVATIO and certain other medicines may affect each other and can cause side effects.

Especially tell your healthcare provider if you or your child take:

- nitrates or guanylate cyclase stimulators. See “What is the most important information I should know about REVATIO?”
- medicines to treat high blood pressure
- medicines for erectile dysfunction (impotence). REVATIO contains sildenafil, which is the same medicine found in another medicine called VIAGRA®. VIAGRA is used for the treatment of erectile dysfunction. Do not take VIAGRA or other PDE-5 inhibitors during treatment with REVATIO.

Ask your healthcare provider or pharmacist for a list of these medicines if you are not sure.

Know the medicines you or your child take. Keep a list of your or your child’s medicines and show it to your healthcare provider and pharmacist when you get a new medicine.

How should I take REVATIO?

- Take or give REVATIO exactly as your healthcare provider tells you.
- Your healthcare provider may change your or your child’s dose of REVATIO as needed. Do not change your dose or stop taking REVATIO without talking to your healthcare provider.
- REVATIO may be prescribed to you as REVATIO tablets or REVATIO oral suspension.
- Take your prescribed dose of REVATIO tablets or oral suspension 3 times a day.
- See the detailed Instructions for Use that comes with REVATIO oral suspension for information on how to take or give REVATIO oral suspension. REVATIO oral suspension will be mixed for you by your pharmacist. Do not mix REVATIO oral suspension with other medicine or flavoring.
- If you or your child take too much REVATIO, call your healthcare provider or go to the nearest hospital emergency room right away.

What are the possible side effects of REVATIO?

REVATIO may cause serious side effects, including:

- See “What is the most important information I should know about REVATIO?”
- Decreased blood pressure. REVATIO may cause low blood pressure that last for a short time. If you take medicines to treat high blood pressure, your healthcare provider should monitor your blood pressure during treatment with REVATIO.
- Decreased eyesight or permanent loss of vision in one or both eyes can be a sign of non-arteritic anterior ischemic optic neuropathy (NAION). Most people who develop NAION have certain risk factors. You can ask your healthcare provider if you have questions about risk factors for NAION. If you notice a sudden decrease or loss of vision in one or both eyes during treatment with REVATIO, contact your healthcare provider right away.
- Sudden decrease or loss of hearing, sometimes with ringing in the ears and dizziness. If you notice a sudden decrease or loss of hearing during treatment with REVATIO, contact your healthcare provider right away.
- In men, an erection that lasts for more than 4 hours (priapism). If you have an erection, with or without pain, that lasts more than 4 hours, contact your healthcare provider or get emergency medical help right away. A painful erection that lasts more than 6 hours must be treated right away or you can have lasting damage to your penis, including the inability to have erections.

The most common side effects of REVATIO in adults include:

- nosebleeds
- headache
- upset stomach
- getting red or hot in the face (flushing)
- arm or leg pain

- muscle aches and pain
- back pain
- diarrhea

The most common side effect of REVATIO in children is an erection that lasts for more than 4 hours (priapism).

These are not all the possible side effects of REVATIO.

Call your doctor for medical advice about side effects. You may report side effects to FDA at 1‑800-FDA-1088.

How should I store REVATIO?

- Store REVATIO tablets at room temperature between 68°F to 77°F (20°C to 25°C).
- Store mixed (reconstituted) REVATIO oral suspension below 86°F (30°C) or in a refrigerator between 36°F to 46°F (2°C to 8°C).
- Do not freeze mixed REVATIO oral suspension.
- Throw away (discard) any remaining REVATIO oral suspension 60 days after mixed by the pharmacist. See the “Discard after” date written on the bottle label.

Keep REVATIO and all medicines out of the reach of children.

General information about the safe and effective use of REVATIO.

Medicines are sometimes prescribed for purposes other than those listed in a Patient Information leaflet. Do not use REVATIO for a condition for which it was not prescribed. Do not give REVATIO to other people, even if they have the same symptoms that you have. It may harm them. You can ask your healthcare provider or pharmacist for information about REVATIO that is written for health professionals.

What are the ingredients in REVATIO?

Active ingredients: sildenafil citrate

Inactive ingredients:

REVATIO tablets: anhydrous dibasic calcium phosphate, croscarmellose sodium, hypromellose, lactose monohydrate, magnesium stearate, microcrystalline cellulose, titanium dioxide, and triacetin

REVATIO oral suspension: citric acid anhydrous, colloidal silicon dioxide anhydrous, grape flavor, sodium benzoate, sodium citrate dihydrate, sorbitol, sucralose, titanium dioxide, and xanthan gum

Distributed by:

Viatris Specialty LLC

Morgantown, WV 26505 U.S.A.

© 2024 Viatris Inc.

REVATIO is a registered trademark of Viatris Specialty LLC, a Viatris Company.

UPJ:PL:RVTTOSI:R2

For more information call Viatris at 1-877-446-3679 (1-877-4-INFO-RX).

This Patient Information has been approved by the U.S. Food and Drug Administration. Revised: December 2024

Instructions for Use

REVATIO® (re-VAH-tee-oh)
(sildenafil)
oral suspension

Read this Instructions for Use before you start taking REVATIO oral suspension or giving REVATIO oral suspension to your child and each time you get a refill. There may be new information. This information does not take the place of talking to your healthcare provider about your or your child’s medical condition or treatment.

Important information:

- Ask your healthcare provider or pharmacist to show you how to measure and take or give your child’s prescribed dose of REVATIO oral suspension.
- Your pharmacist will mix (reconstitute) REVATIO oral suspension before it is given to you. Do not take or give REVATIO oral suspension and contact your pharmacist if the medicine in the bottle is still a powder.
- Always use the oral dosing syringe that comes with REVATIO oral suspension. If your carton does not come with an oral dosing syringe, contact your pharmacist.
- Do not take or give REVATIO oral suspension if the bottle adaptor is not in the bottle. If the bottle adaptor is not in the bottle, contact your pharmacist.
- REVATIO oral suspension should not be mixed with any other medicine or flavoring.

Supplies you will need to take or give a dose of REVATIO oral suspension (See Figure A):

- 1 bottle of REVATIO oral suspension with pre-inserted bottle adaptor
- 1 oral dosing syringe (provided in the carton)

Step 1. Shake the bottle of REVATIO oral suspension for 10 seconds before each use. (See Figure B)

Step 2. Remove the cap. Open the bottle by pushing down on the cap and twisting it in the direction of the arrow (counter-clockwise). (See Figure C)

Step 3. Fully push down (depress) the plunger of the oral dosing syringe. Then insert the tip of the oral dosing syringe into the bottle adaptor while holding the bottle upright, on a flat surface. (See Figure D)

Step 4. Turn the bottle upside down while holding the oral dosing syringe in place. Slowly pull back the plunger of the oral dosing syringe until the bottom of the plunger is even with the mL marking on the syringe for your or your child’s prescribed dose. (See Figure E)
If your or your child’s dose of REVATIO oral suspension is more than 2 mL (20 mg), you will need to divide the dose. Follow the instructions given to you by your healthcare provider or pharmacist about how to prepare the divided dose.

If you see air bubbles in the oral dosing syringe, slowly push the plunger all the way up so that REVATIO oral suspension flows back into the bottle and repeat Step 4.

Step 5. Turn the bottle back upright with the oral dosing syringe still in place. Place the bottle on a flat surface. Remove the oral dosing syringe from the bottle adaptor by pulling straight up on the barrel of the oral dosing syringe. (See Figure F) Do not press on the plunger of the oral dosing syringe at this time.

Step 6. Put the tip of the oral dosing syringe into your or your child’s mouth and point it towards the inside of the cheek. Slowly push the plunger of the oral dosing syringe all the way down to give the entire dose. Do not squirt the medicine out quickly. (See Figure G)
If you are giving REVATIO oral suspension to a child, make sure they are in an upright position before giving the medicine.

Step 7. Replace the cap on the bottle, leaving the bottle adaptor in place. Turn the cap in the direction of the arrow (clockwise) to close the bottle. (See Figure H)

Step 8. Wash the oral dosing syringe after each use. Pull the plunger out of the barrel and rinse both parts with water. (See Figure I)

Step 9. Dry all parts with a clean paper towel. Push the plunger back into the barrel. Store the oral dosing syringe with the REVATIO oral suspension bottle.

How should I store REVATIO?

- Store mixed (reconstituted) REVATIO oral suspension below 86°F (30°C) or in a refrigerator between 36°F to 46°F (2°C to 8°C).
- Do not freeze mixed REVATIO oral suspension.
- Throw away (discard) any remaining REVATIO oral suspension 60 days after mixed by the pharmacist. See the “Discard after” date written on the bottle label.

Keep REVATIO and all medicines out of the reach of children.

Distributed by:
Viatris Specialty LLC
Morgantown, WV 26505 U.S.A.

© 2024 Viatris Inc.

REVATIO is a registered trademark of Viatris Specialty LLC, a Viatris Company.

UPJ:IFU:RVTTOSI:R2

This Instructions for Use has been approved by the U.S. Food and Drug Administration. Revised: December 2024

PRINCIPAL DISPLAY PANEL – 20 mg

NDC 58151-402-77

Revatio®
(sildenafil)
tablets

20 mg*

Rx only

90 Tablets

Store at controlled room
temperature 20°C to 25°C (68°F
to 77°F); excursions permitted
to 15°C to 30°C (59°F to 86°F)
[see USP Controlled Room
Temperature].

Dispense in tight containers
(USP).

DOSAGE AND USE
See accompanying prescribing
information.

*Each tablet contains sildenafil
citrate equivalent to 20 mg
sildenafil.

Distributed by:
Viatris Specialty LLC
Morgantown, WV 26505 U.S.A.

© 2024 Viatris Inc.

Made in France

RUPJ402MM

PRINCIPAL DISPLAY PANEL – 10 mg/12.5 mL

NDC 58151-395-31

Sterile Single-dose
Vial

Rx only

Revatio®
(sildenafil) Injection

10 mg/12.5 mL
(0.8 mg/mL)

For Intravenous Use
Sterile Single-dose Vial,
Discard Unused Portion

Store at controlled room
temperature 20°C to 25°C (68°F
to 77°F); excursions permitted
to 15°C to 30°C (59°F to 86°F)
[see USP Controlled Room
Temperature].

Each mL of solution contains
1.124 mg sildenafil citrate,
50.5 mg dextrose and
Water for Injection.

DOSAGE AND USE
See accompanying prescribing
information.

Distributed by:
Viatris Specialty LLC
Morgantown, WV 26505 U.S.A.

© 2024 Viatris Inc.

REVATIO is a registered trademark
of Viatris Specialty LLC, a Viatris
Company.

Made in France

UPJ:395:1C:R1

PRINCIPAL DISPLAY PANEL – 10 mg/mL

NDC 58151-385-35

Rx only

Revatio®
(sildenafil) for
oral suspension

10 mg/mL

For Oral Use Only

Shake Well Before Each Use

RECONSTITUTION DIRECTIONS:
Gently tap the bottle to loosen the
powder. The total volume of water to
be added is 90 mL. Add 60 mL of
water and shake vigorously for at
least 30 seconds. Add another 30 mL
of water and shake for at least
another 30 seconds to obtain a
uniform suspension.

112 mL following Reconstitution

Grape Flavored

Rx only

BEFORE RECONSTITUTION:
Recommended storage for Revatio powder
for oral suspension: Store below 30°C
(86°F) in the original package in order to
protect from moisture.

RECONSTITUTED SUSPENSION:
Store below 30°C (86°F) or in refrigerator
at 2°C to 8°C (36°F to 46°F). Do not freeze.
Discard any unused portion 60 days after
reconstitution.

Each mL of the suspension contains 10 mg
of sildenafil (as citrate) when reconstituted
with 90 mL water.

Each bottle contains 1.57 g of sildenafil
citrate (1.12 g sildenafil).

RECOMMENDED DOSAGE: See prescribing
information.
An oral dosing syringe, and a press-in bottle
adaptor are also provided.

Distributed by:
Viatris Specialty LLC
Morgantown, WV 26505 U.S.A.

© 2024 Viatris Inc.

REVATIO is a registered trademark of Viatris
Specialty LLC, a Viatris Company.

Made in France

UPJ:385:1C:R1